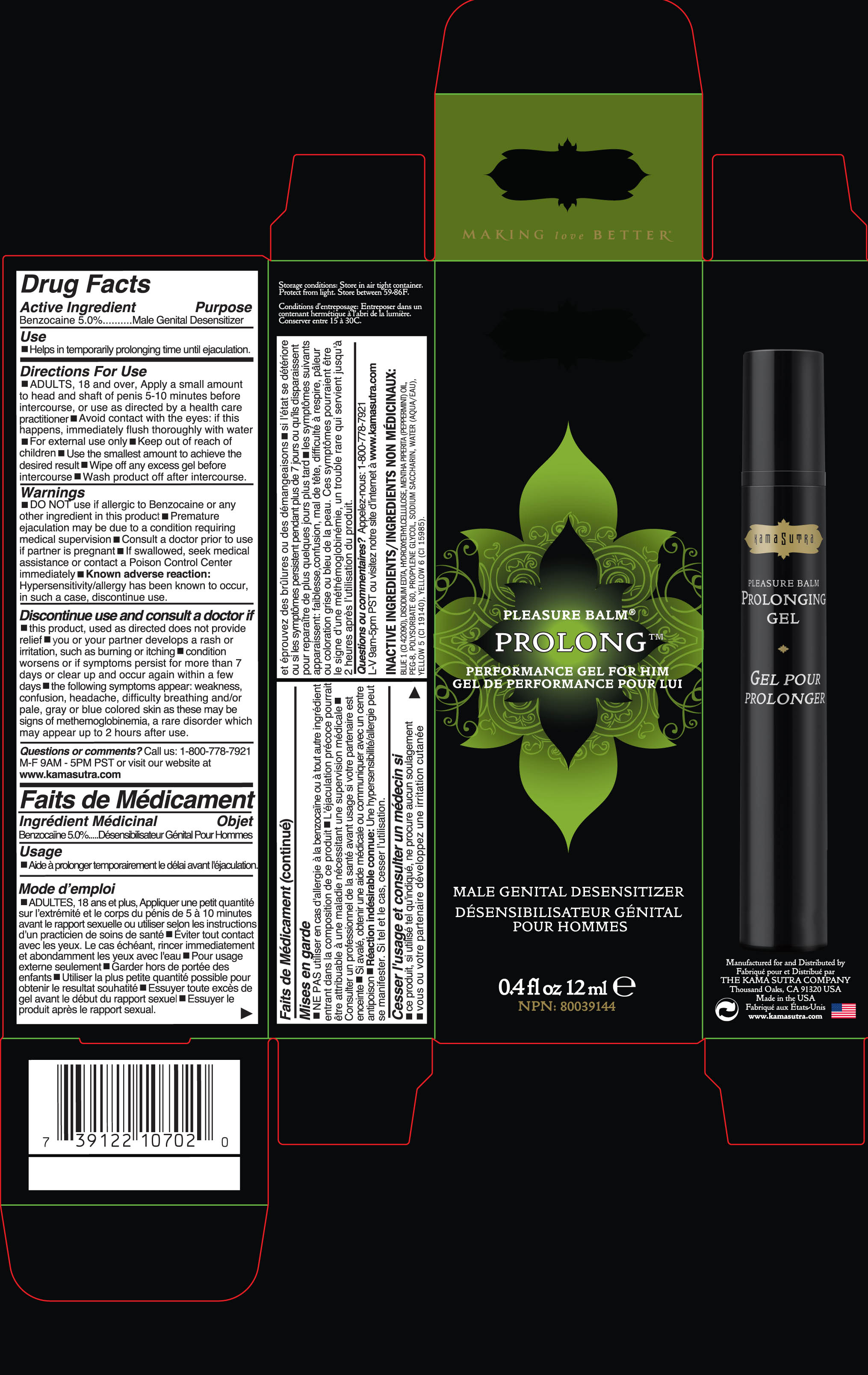 DRUG LABEL: Pleasure Balm
NDC: 56152-1470 | Form: GEL
Manufacturer: Cosmetic Enterprises Ltd
Category: otc | Type: HUMAN OTC DRUG LABEL
Date: 20251014

ACTIVE INGREDIENTS: BENZOCAINE 5 g/100 mL
INACTIVE INGREDIENTS: FD&C BLUE NO. 1; EDETATE DISODIUM; CETYL HYDROXYETHYLCELLULOSE (350000 MW); MENTHA PIPERITA; POLYETHYLENE GLYCOL 400; POLYSORBATE 60; PROPYLENE GLYCOL; SACCHARIN SODIUM; WATER; FD&C YELLOW NO. 5; FD&C YELLOW NO. 6

Pleasure Balm

Active Ingredients Purpose

Benzocaine 5.0 % Male genital desensitizer

Use

Helps in temporarily prolonging time until ejaculation

Keep out of reach of children.

INDICATIONS AND USAGE

Discontinue use and consult a doctor if

This product, used as directed does not provide relief

You or your partner develops a rash or irritation, such as burning or itching

Condition worsens or if symptoms persist for more than 7 days or clear up and occur again within a few days

The following symptoms appear: weakness, confusion, headache, difficulty breathing and/or pale, gray or blue colored skin as these may be signs of methemoglobinemia, a rare disorder which may appear up to 2 hours of use

Warnings

DO NOT use if allergic to Benzocaine or any other ingredient in this product

If swallowed seek medical assistance or contact a poison control or contact a poison control Center right away.

Premature ejaculation may be due to condition requiring medical supervision

Consult a doctor prior to use if partner is pregnant

Avoid contact with eyes: if this happens, rinse thoroughly with water

Known adverse reactions Hypersensitivity/allergy has been known to occur, in such a case, discontinue use.

DOSAGE AND ADMINISTRATION

Directions for use

Adults, 18 and over. Apply a small amount to head and shaft of penis 5-10 minutes before intercourse, or use as directed by a health care practitioner. Use the smallest amount to achieve the desired result. Wipe off any excess gel before intercourse. Wash product off after intercourse. For external Use only.

INACTIVE INGREDIENT

Inactive Inagredients: Blue 1 (CI 42090), Disodium EDTA, Hydroxyethylcellulose, Mentha Piperita (peppermint oil), PEG-8, Polysorbate 60, Propylene Glycol, Sodium Saccharin, Water (Aqua/Eau), Yellow 5 (CI 19140), Yellow 6 (CI 15985)

PACKAGE LABEL

Pleasure Balm

Prolonging Gel for Men

Male Genital Desensitizer

Desensibilisateur Genital Pour hommes

0.4 fl oz 12 ml